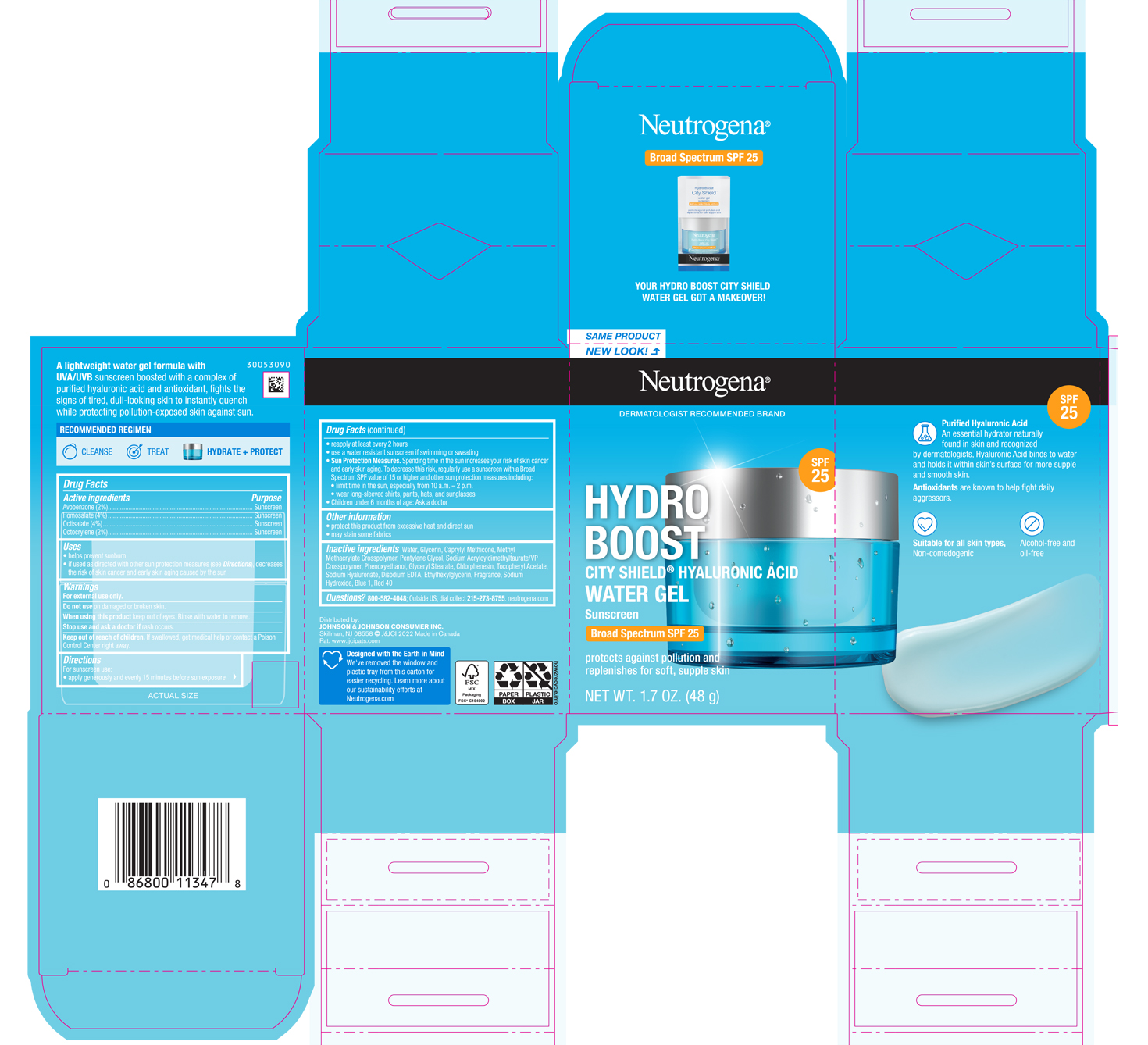 DRUG LABEL: Neutrogena Hydro Boost City Shield water Broad Spectrum SPF 25
NDC: 69968-0397 | Form: GEL
Manufacturer: Kenvue Brands LLC
Category: otc | Type: HUMAN OTC DRUG LABEL
Date: 20250805

ACTIVE INGREDIENTS: AVOBENZONE 20 mg/1 g; HOMOSALATE 40 mg/1 g; OCTISALATE 40 mg/1 g; OCTOCRYLENE 20 mg/1 g
INACTIVE INGREDIENTS: GLYCERIN; CAPRYLYL TRISILOXANE; METHYL METHACRYLATE/GLYCOL DIMETHACRYLATE CROSSPOLYMER; PENTYLENE GLYCOL; PHENOXYETHANOL; GLYCERYL MONOSTEARATE; CHLORPHENESIN; HYALURONATE SODIUM; EDETATE DISODIUM ANHYDROUS; .ALPHA.-TOCOPHEROL ACETATE; ETHYLHEXYLGLYCERIN; SODIUM HYDROXIDE; FD&C BLUE NO. 1; FD&C RED NO. 40; WATER

Neutrogena® Hydro Boost City Shield™ water gel BROAD SPECTRUM SPF 25

Drug Facts

ACTIVE INGREDIENT

Active Ingredients | Purpose
Avobenzone (2%) | Sunscreen
Homosalate (4%) | Sunscreen
Octisalate (4%) | Sunscreen
Octocrylene (2%) | Sunscreen

Uses

- helps prevent sunburn
- if used as directed with other sun protection measures (see Directions), decreases the risk of skin cancer and early skin aging caused by the sun

Warnings

For external use only.

Do not use on damaged or broken skin.

When using this product keep out of eyes. Rinse with water to remove.

Stop use and ask a doctor if rash occurs.

Keep out of reach of children. If swallowed, get medical help or contact a Poison Control Center right away.

Directions

For sunscreen use:

- apply generously and evenly 15 minutes before sun exposure
- reapply at least every 2 hours
- use a water resistant sunscreen if swimming or sweating
- Sun Protection Measures. Spending time in the sun increases your risk of skin cancer and early skin aging. To decrease this risk, regularly use a sunscreen with a Broad Spectrum SPF value of 15 or higher and other sun protection measures including:
  - limit time in the sun, especially from 10 a.m. – 2 p.m.
  - wear long-sleeved shirts, pants, hats, and sunglasses
- children under 6 months of age: Ask a doctor

Other Information

- protect this product from excessive heat and direct sun
- may stain some fabrics

Inactive ingredients

Water, Glycerin, Caprylyl Methicone, Methyl Methacrylate Crosspolymer, Pentylene Glycol, Sodium Acryloyldimethyltaurate/VP Crosspolymer, Phenoxyethanol, Glyceryl Stearate, Chlorphenesin, Tocopheryl Acetate, Sodium Hyaluronate, Disodium EDTA, Ethylhexylglycerin, Fragrance, Sodium Hydroxide, Blue 1, Red 40

Questions?

800-582-4048; Outside US, dial collect 215-273-8755. neutrogena.com

Distributed by:
JOHNSON & JOHNSON CONSUMER INC.
Skillman, NJ 08558

PRINCIPAL DISPLAY PANEL - 48 g Jar Carton

SAME PRODUCT

NEW LOOK!

Neutrogena®

DERMATOLOGIST RECOMMENDED BRAND

SPF

25

HYDRO BOOST

CITY SHIELD® HYALURONIC ACID

WATER GEL

Sunscreen

Broad Spectrum SPF 25

protects against pollution and

replenishes for soft, supple skin

NET WT. 1.7 OZ. (48 g)